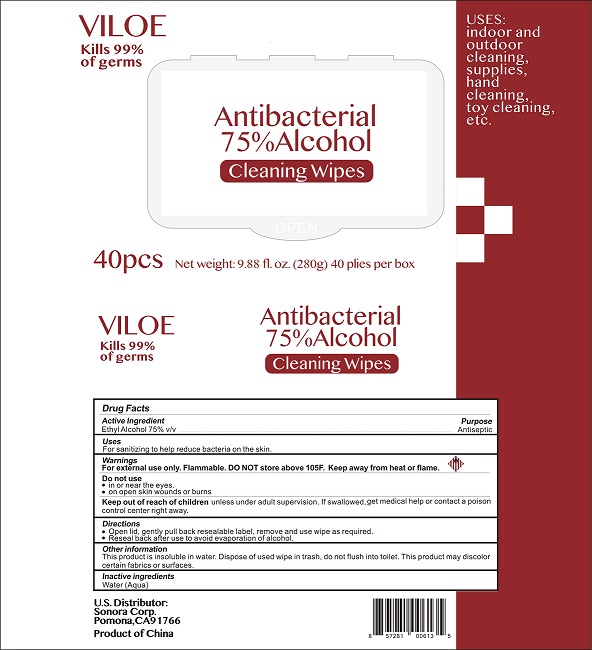 DRUG LABEL: VILOE
NDC: 78733-001 | Form: CLOTH
Manufacturer: Sonora Corporation
Category: otc | Type: HUMAN OTC DRUG LABEL
Date: 20200603

ACTIVE INGREDIENTS: ALCOHOL 75 mL/100 mL
INACTIVE INGREDIENTS: WATER

Active Ingredient

Ethyl Alcohol 75% v/v.

Purpose

Antiseptic

Uses

For sanitizing to help reduce bacteria on the skin.

Warnings

For external use only. Flammable. DO NOT store above 105^0F. Keep away from heat or flame.

Do not use

- in or near the eyes.
- on open skin wounds or burns.

Keep out of reach of children, unless under adult supervision. If swallowed, get medical help or contact a Poison Control Center right away.

Directions

- Open lid, gently pull back resealable label, remove and use wipe as required.
- Reseal back after use to avoid evaporation of alcohol.

Other information
This product is insoluble in water. Dispose of used wipe in trash, do not flush into toilet. This product may discolor certain fabrics or surfaces.

Inactive ingredients

Water (Aqua)